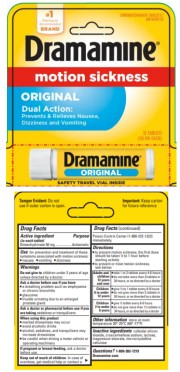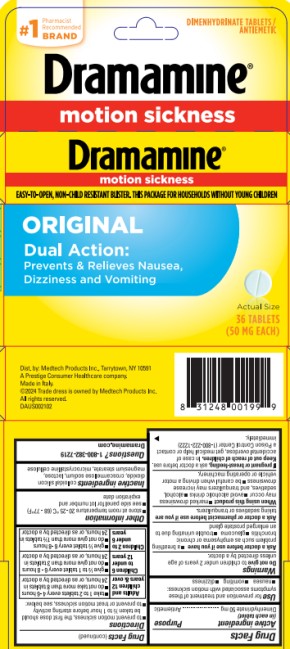 DRUG LABEL: Dramamine Original Formula
NDC: 63029-901 | Form: TABLET
Manufacturer: Medtech Products Inc.
Category: otc | Type: HUMAN OTC DRUG LABEL
Date: 20251023

ACTIVE INGREDIENTS: DIMENHYDRINATE 50 mg/1 1
INACTIVE INGREDIENTS: SILICON DIOXIDE; CROSCARMELLOSE SODIUM; LACTOSE, UNSPECIFIED FORM; MAGNESIUM STEARATE; CELLULOSE, MICROCRYSTALLINE

Dramamine Original Formula

Drug Facts

Active ingredient

(in each tablet)

Dimenhydrinate 50 mg

Purpose

Antiemetic

Use

for prevention and treatment of these symptoms associated with motion sickness:

- nausea
- vomiting
- dizziness

Warnings

Do not give to

children under 2 years of age unless directed by a doctor.

Ask a doctor before use if you have

- a breathing problem such as emphysema or chronic bronchitis
- glaucoma
- trouble urinating due to an enlarged prostate gland

Ask a doctor or pharmacist before use if you are

taking sedatives or tranquilizers.

When using this product

- marked drowsiness may occur
- avoid alcoholic drinks
- alcohol, sedatives, and tranquilizers may increase dizziness
- be careful when driving a motor vehicle or operating machinery

If pregnant or breast-feeding,

ask a doctor before use.

Keep out of reach of children.

In case of overdose, get medical help or contact a Poison Control Center (1-800-222-1222) immediately.

Directions

- to prevent motion sickness, the first dose should be taken ½ to 1 hour before starting activity
- to prevent or treat motion sickness, see below:

Adults and children 12 years and over | - take 1 to 2 tables every 4-6 hours - do not take more than 8 tablets in 24 hours, or as directed by a doctor
Children 6 to under 12 years | - give ½ to 1 tablet every 6-8 hours - do not give more than 3 tablets in 24 hours, or as directed by a doctor
Children 2 to under 6 years | - give ½ tablet every 6-8 hours - do not give more than 1 ½ tablets in 24 hours, or as directed by a doctor

Other information

- store at room temperature 20-25ºC (68-77ºF)

Inactive ingredients

colloidal silicon dioxide, croscarmellose sodium, lactose, magnesium stearate, microcrystalline cellulose

Questions or comments?

Call 1-800-382-7219

Dramamine.com

PRINCIPAL DISPLAY PANEL

Dramamine®
motion sickness
Original
Dimenhydrinate tablets/antiemetic
12 tablets (50 mg each)

PRINCIPAL DISPLAY PANEL

Dramamine®
motion sickness
Original
Dimenhydrinate tablets/antiemetic
36 tablets (50 mg each)